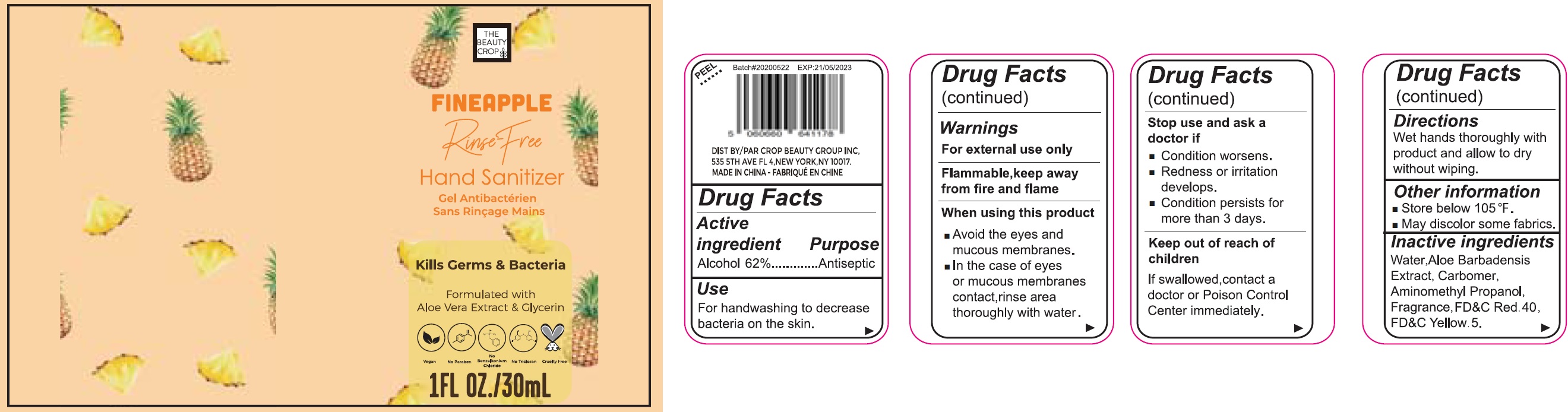 DRUG LABEL: FINEAPPLE Hand Sanitizer
NDC: 78768-002 | Form: GEL
Manufacturer: CROP BEAUTY GROUP INC.
Category: otc | Type: HUMAN OTC DRUG LABEL
Date: 20231026

ACTIVE INGREDIENTS: ALCOHOL 0.62 mL/1 mL
INACTIVE INGREDIENTS: WATER; CARBOMER HOMOPOLYMER, UNSPECIFIED TYPE; AMINOMETHYLPROPANOL; FD&C RED NO. 40; FD&C YELLOW NO. 5

FINEAPPLE Hand Sanitizer

Active ingredient

Alcohol 62%

Purpose

Antiseptic.

Use

For handwashing to decrease bacteria on the skin.

Warnings

For external use only

Flammable, keep away from fire and flame

When using this product

- Avoid the eyes and mucous membranes.
- In the case of eyes or mucous membranes contact,rinse area thoroughly with water.

Stop use and ask a doctor if

- Condition worsens.
- Redness or irritation develops.
- Condition persists for more than 3 days.

Keep out of reach of children.

If swallowed,contact a doctor or Poison Control Center immediately.

Directions

Wet hands thoroughly with product and allow to dry without wiping.

Other information

- Store below 105 °F.
- May discolor some fabrics.

Inactive ingredients

Water,Aloe Barbadensis Extract, Carbomer, Aminomethyl Propanol, Fragrance, FD&C Red 40, FD&C Yellow 5.